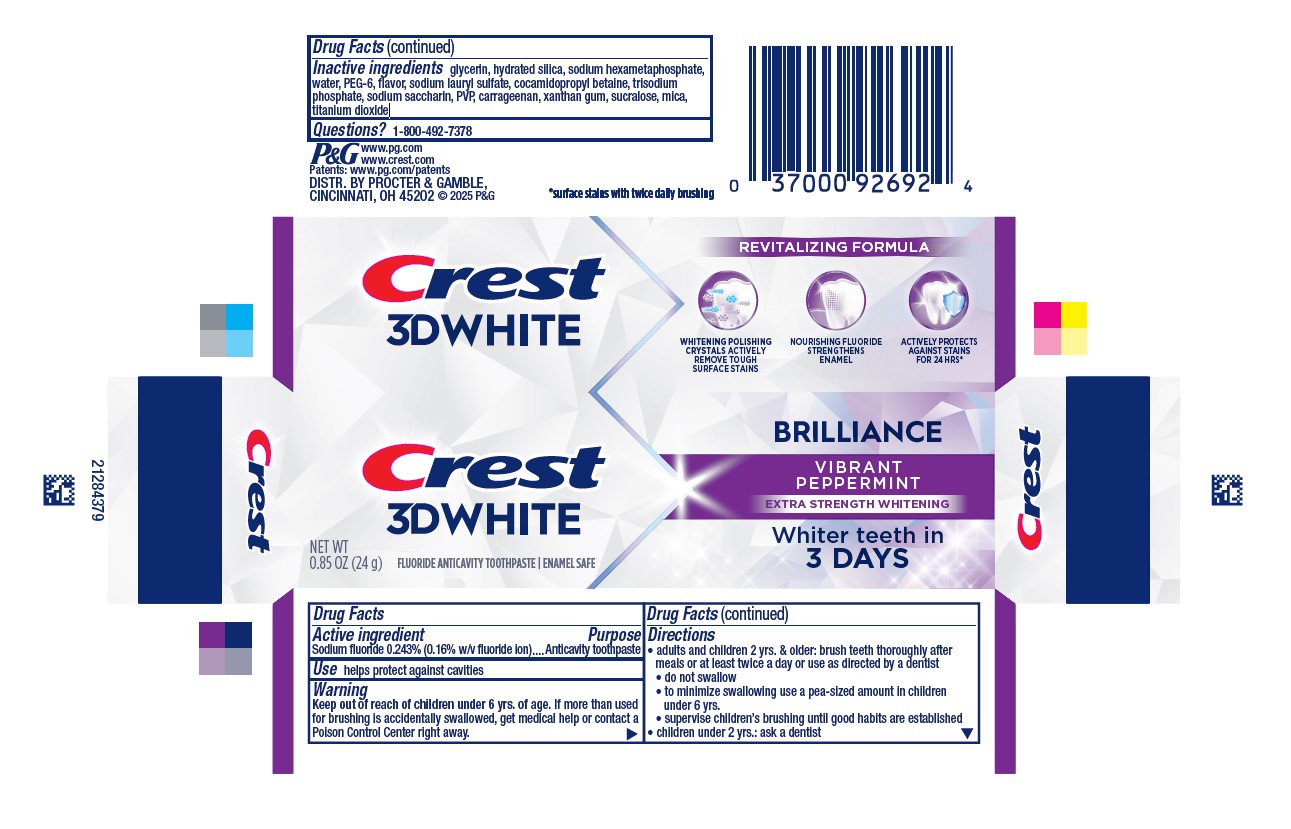 DRUG LABEL: Crest 3D White
NDC: 37000-873 | Form: PASTE, DENTIFRICE
Manufacturer: The Procter & Gamble Manufacturing Company
Category: otc | Type: HUMAN OTC DRUG LABEL
Date: 20250604

ACTIVE INGREDIENTS: SODIUM FLUORIDE 1.6 mg/1 g
INACTIVE INGREDIENTS: XANTHAN GUM; SUCRALOSE; MICA; TITANIUM DIOXIDE; GLYCERIN; HYDRATED SILICA; SODIUM POLYMETAPHOSPHATE; WATER; SACCHARIN SODIUM; POLYETHYLENE GLYCOL 300; SODIUM PHOSPHATE, TRIBASIC, ANHYDROUS; SODIUM LAURYL SULFATE; CARRAGEENAN; COCAMIDOPROPYL BETAINE

Crest® 3D White™
Brilliance Vibrant Peppermint

Drug Facts

Active ingredient

Sodium fluoride 0.243% (0.16% w/v fluoride ion)

Purpose

Anticavity toothpaste

Use

helps protect against cavities

Warning

Keep out of reach of children under 6 yrs. of age. If more than used for brushing is accidentally swallowed, get medical help or contact a Poison Control Center right away.

Directions

- adults and children 2 yrs. & older: brush teeth thoroughly after meals or at least twice a day or use as directed by a dentist
- do not swallow
- to minimize swallowing use a pea-sized amount in children under 6
- supervise children's brushing until good habits are established
- children under 2 yrs.: ask a dentist

Inactive ingredients

glycerin, hydrated silica, sodium hexametaphosphate, water, PEG-6, flavor, trisodium phosphate, sodium lauryl sulfate, carrageenan, cocamidopropyl betaine, sodium saccharin, PEG-20M or PEG-23M, xanthan gum, sucralose, mica, titanium dioxide

Questions?

1-800-492-7378

DISTR. BY PROCTER & GAMBLE,
CINCINNATI, OH 45202

PRINCIPAL DISPLAY PANEL - 24g Tube Carton

CREST 3D WHITE

BRILLIANCE

VIBRANT PEPPERMINT

EXTRA STRENGTH WHITENING

WHITER TEETH IN 3 DAYS

NET WT 0.85OZ (24 g)

FLUORIDE ANTICAVITY TOOTHPASTE

ENAMEL SAFE